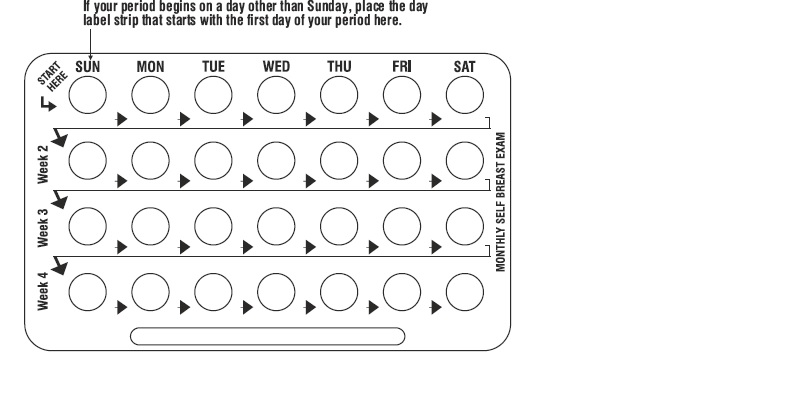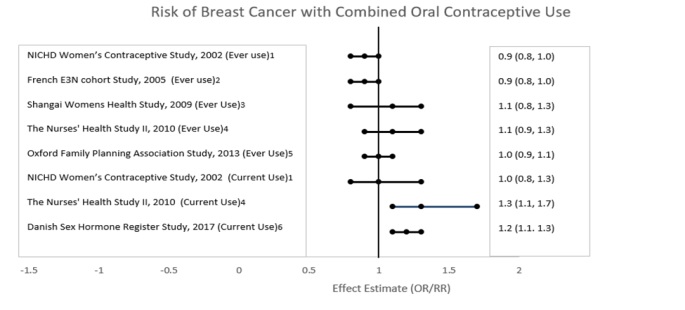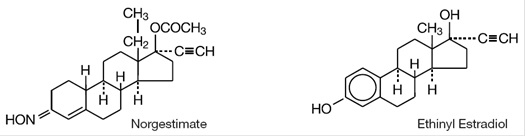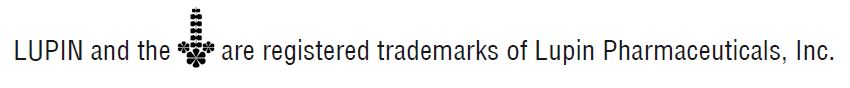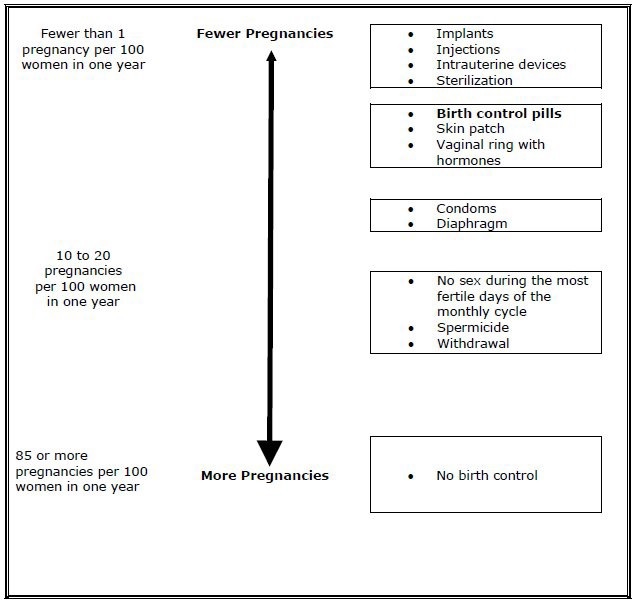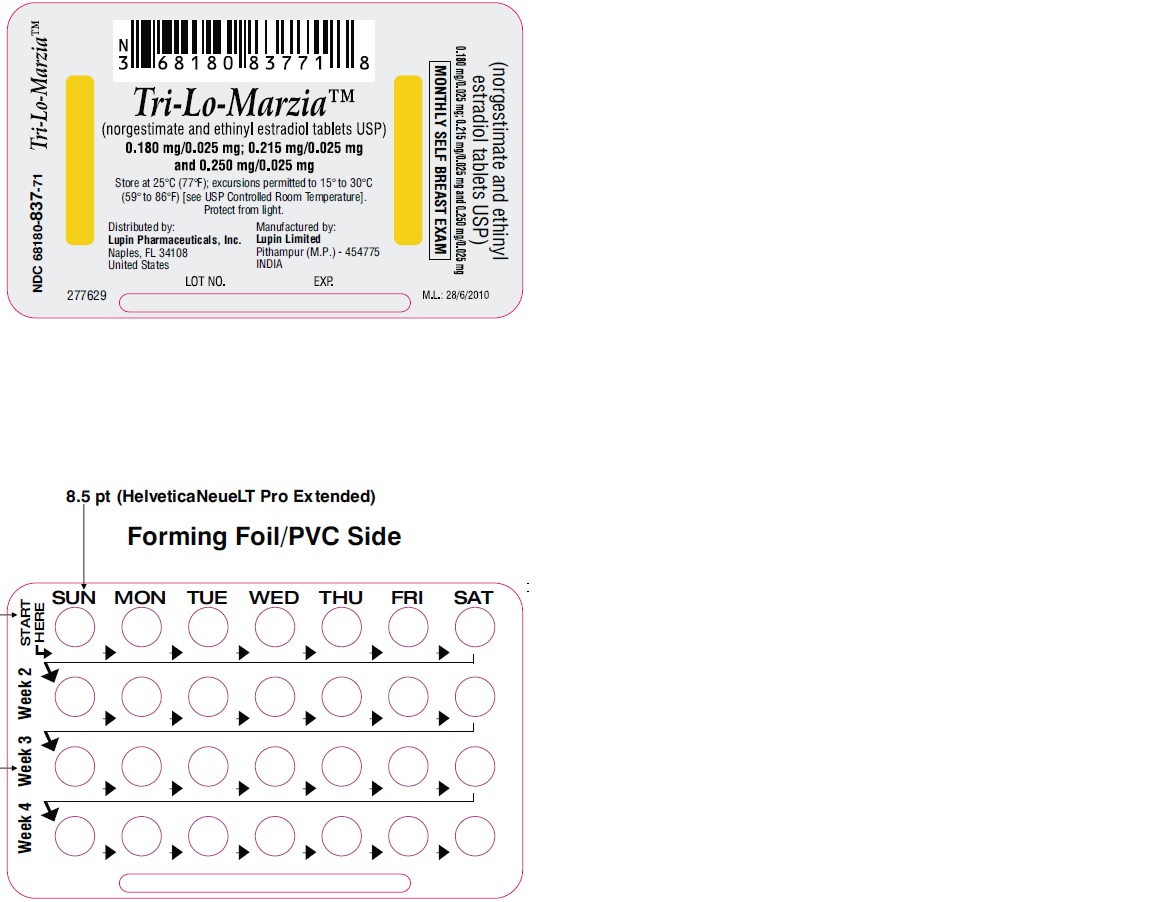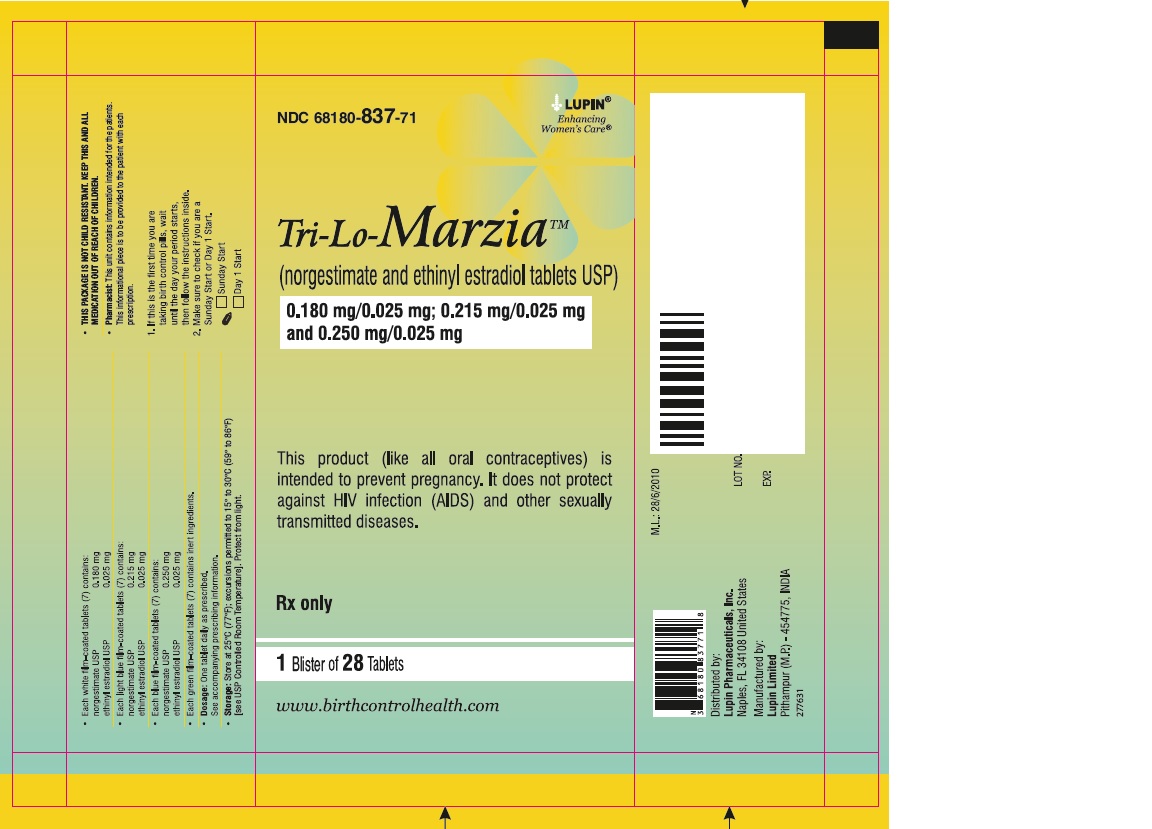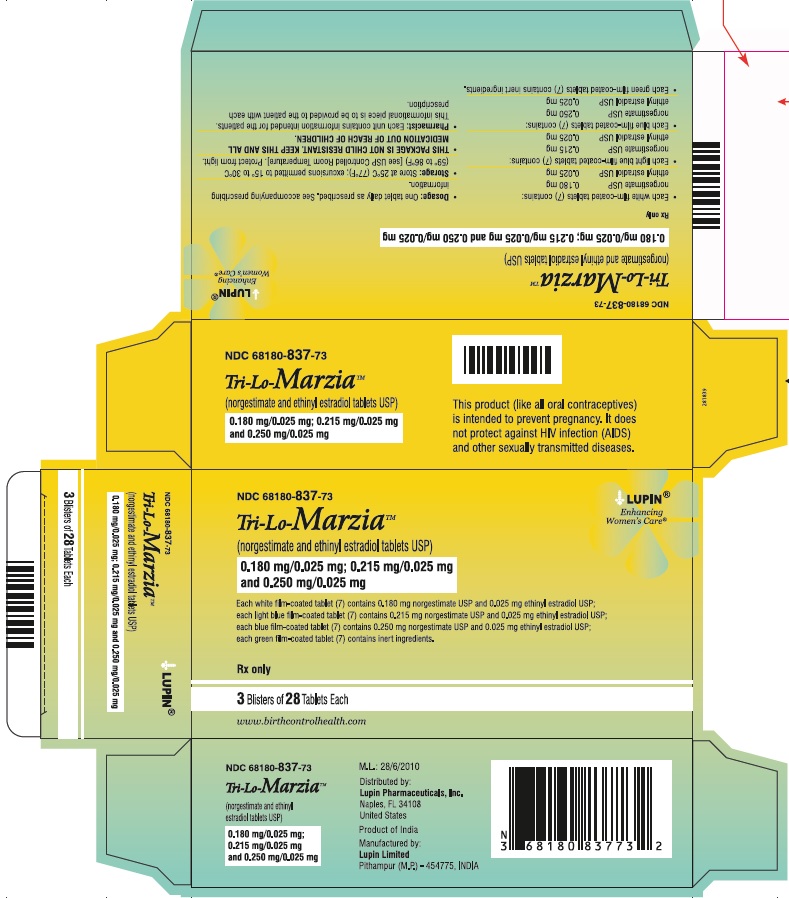 DRUG LABEL: TRI-LO-MARZIA

NDC: 68180-837 | Form: KIT | Route: ORAL
Manufacturer: Lupin Pharmaceuticals, Inc.
Category: prescription | Type: HUMAN PRESCRIPTION DRUG LABEL
Date: 20251209

ACTIVE INGREDIENTS: ETHINYL ESTRADIOL 0.025 mg/1 1; NORGESTIMATE 0.18 mg/1 1; ETHINYL ESTRADIOL 0.025 mg/1 1; NORGESTIMATE 0.215 mg/1 1; ETHINYL ESTRADIOL 0.025 mg/1 1; NORGESTIMATE 0.25 mg/1 1
INACTIVE INGREDIENTS: ANHYDROUS LACTOSE; CELLULOSE, MICROCRYSTALLINE; CROSCARMELLOSE SODIUM; HYPROMELLOSES; LACTOSE MONOHYDRATE; MAGNESIUM STEARATE; POLYETHYLENE GLYCOL 400; POVIDONE; TITANIUM DIOXIDE; ALUMINUM OXIDE; ANHYDROUS LACTOSE; CELLULOSE, MICROCRYSTALLINE; CROSCARMELLOSE SODIUM; FD&C BLUE NO. 2; HYPROMELLOSES; LACTOSE MONOHYDRATE; MAGNESIUM STEARATE; POLYETHYLENE GLYCOL 400; POVIDONE; TITANIUM DIOXIDE; ALUMINUM OXIDE; ANHYDROUS LACTOSE; CELLULOSE, MICROCRYSTALLINE; CROSCARMELLOSE SODIUM; FD&C BLUE NO. 2; HYPROMELLOSES; LACTOSE MONOHYDRATE; MAGNESIUM STEARATE; POLYETHYLENE GLYCOL 400; POVIDONE; TITANIUM DIOXIDE; CROSCARMELLOSE SODIUM; FD&C BLUE NO. 2; FERRIC OXIDE YELLOW; HYPROMELLOSES; POLYETHYLENE GLYCOL 400; CELLULOSE, MICROCRYSTALLINE; LACTOSE MONOHYDRATE; MAGNESIUM STEARATE; TITANIUM DIOXIDE

HIGHLIGHTS OF PRESCRIBING INFORMATION

These highlights do not include all the information needed to use TRI-LO-MARZIA safely and effectively. See full prescribing information for TRI-LO-MARZIA. TRI-LO-MARZIA&trade; (norgestimate and ethinyl estradiol tablets USP), for oral use Initial U.S. Approval: 1989

WARNING: CIGARETTE SMOKING and SERIOUS CARDIOVASCULAR EVENTS

See full prescribing information for complete boxed warning.

- Tri-Lo-Marzia is contraindicated in women over 35 years old who smoke. (4)
- Cigarette smoking increases the risk of serious cardiovascular events from combination oral contraceptives (COC) use. (4)

RECENT MAJOR CHANGES

Warnings and Precautions (5.11) 12/2021

1 INDICATIONS AND USAGE

Tri-Lo-Marzia is an estrogen/progestin COC, indicated for use by women to prevent pregnancy. (1.1)

2 DOSAGE AND ADMINISTRATION

- Take one tablet daily by mouth at the same time every day. (2.2)
- Take tablets in the order directed on the blister. (2.2)
- Do not skip or delay tablet intake. (2.2)

3 DOSAGE FORMS AND STRENGTHS

Tri-Lo-Marzia consists of 28 round, film-coated tablets in the following order (3):

- 7 white to off white tablets each containing 0.18 mg norgestimate and 0.025 mg ethinyl estradiol
- 7 light blue tablets each containing 0.215 mg norgestimate and 0.025 mg ethinyl estradiol
- 7 blue tablets each containing 0.25 mg norgestimate and 0.025 mg ethinyl estradiol
- 7 green tablets (inert)

4 CONTRAINDICATIONS

- A high risk of arterial or venous thrombotic diseases (4)
- Liver tumors or liver disease (4)
- Undiagnosed abnormal uterine bleeding (4)
- Pregnancy (4)
- Current diagnosis of, or history of, breast cancer, which may be hormone-sensitive (4)
- Co-administration with Hepatitis C drug combinations containing ombitasvir/paritaprevir/ritonavir, with or without dasabuvir (4)

5 WARNINGS AND PRECAUTIONS

- Thromboembolic Disorders and Other Vascular Problems: Stop Tri-Lo-Marzia if a thrombotic event occurs. Stop at least 4 weeks before and through 2 weeks after major surgery. Start no earlier than 4 weeks after delivery, in women who are not breastfeeding. (5.1)
- Liver Disease: Discontinue Tri-Lo-Marzia if jaundice occurs. (5.2)
- High Blood Pressure: If used in women with well-controlled hypertension, monitor blood pressure and stop Tri-Lo-Marzia if blood pressure rises significantly. (5.4)
- Carbohydrate and Lipid Metabolic Effects: Monitor prediabetic and diabetic women taking Tri-Lo-Marzia. Consider an alternate contraceptive method for women with uncontrolled dyslipidemia. (5.6)
- Headache: Evaluate significant change in headaches and discontinue Tri-Lo-Marzia if indicated. (5.7)
- Bleeding Irregularities and Amenorrhea: Evaluate irregular bleeding or amenorrhea. (5.8)

6 ADVERSE REACTIONS

The most common adverse reactions reported during clinical trials (≥2%) were: headache/migraine, nausea/vomiting, breast issues, abdominal pain, menstrual disorders, mood disorders, acne, vulvovaginal infection, abdominal distension, weight increased, fatigue. (6.1)

To report SUSPECTED ADVERSE REACTIONS, contact Lupin Pharmaceuticals, Inc. at 1-800-399-2561 or FDA at 1-800-FDA-1088 or www.fda.gov/medwatch.

7 DRUG INTERACTIONS

Drugs or herbal products that induce certain enzymes including CYP3A4, may decrease the effectiveness of COCs or increase breakthrough bleeding. Counsel patients to use a back-up or alternative method of contraception when enzyme inducers are used with COCs. (7.1)

8 USE IN SPECIFIC POPULATIONS

Nursing mothers: Not recommended; can decrease milk production. (8.3)

FULL PRESCRIBING INFORMATION

WARNING: CIGARETTE SMOKING and SERIOUS CARDIOVASCULAR EVENTS

Cigarette smoking increases the risk of serious cardiovascular events from combination oral contraceptive (COC) use. This risk increases with age, particularly in women over 35 years of age, and with the number of cigarettes smoked. For this reason, COCs are contraindicated in women who are over 35 years of age and smoke [see CONTRAINDICATIONS (4)].

1 INDICATIONS AND USAGE

1.1 Oral Contraception

Tri-Lo-Marzia™ Tablets are indicated for use by females of reproductive potential to prevent pregnancy [see CLINICAL STUDIES (14)].

2 DOSAGE AND ADMINISTRATION

2.1 How to Start Tri-Lo-Marzia

Tri-Lo-Marzia is dispensed in a blister [see HOW SUPPLIED/STORAGE AND HANDLING (16)]. Tri-Lo-Marzia may be started using either a Day 1 start or a Sunday start (see Table 1). For the first cycle of a Sunday Start regimen, an additional method of contraception should be used until after the first 7 consecutive days of administration.

2.2 How to Take Tri-Lo-Marzia

Table 1: Instructions for Administration of Tri-Lo-Marzia
Starting COCs in women not currently using hormonal contraception (Day 1 Start or Sunday Start) Important: Consider the possibility of ovulation and conception prior to initiation of this product. Tablet Color: ο Tri-Lo-Marzia active tablets are white to off white (Day 1 to Day 7), light blue (Day 8 to Day 15) and blue (Day 16 to Day 21) and has green inactive tablets (Day 22 to Day 28) | Day 1 Start: ο Take first active tablet without regard to meals on the first day of menses. ο Take subsequent active tablets once daily at the same time each day for a total of 21 days. ο Take one green inactive tablet daily for 7 days and at the same time of day that active tablets were taken. ο Begin each subsequent pack on the same day of the week as the first cycle pack (i.e., on the day after taking the last inactive tablet)
 | Sunday Start: ο Take first active tablet without regard to meals on the first Sunday after the onset of menses. Due to the potential risk of becoming pregnant, use additional non-hormonal contraception (such as condoms and spermicide) for the first seven days of the patient’s first cycle pack of Tri-Lo-Marzia. ο Take subsequent active tablets once daily at the same time each day for a total of 21 days. ο Take one green inactive tablet daily for the following 7 days and at the same time of day that active tablets were taken. ο Begin each subsequent pack on the same day of the week as the first cycle pack (i.e., on the Sunday after taking the last inactive tablet) and additional non-hormonal contraceptive is not needed.
Switching to Tri-Lo-Marzia from another oral contraceptive | Start on the same day that a new pack of the previous oral contraceptive would have started.
Switching from another contraceptive method to Tri-Lo-Marzia | Start Tri-Lo-Marzia:
ο Transdermal patch | ο On the day when next application would have been scheduled
ο Vaginal ring | ο On the day when next insertion would have been scheduled
ο Injection | ο On the day when next injection would have been scheduled
ο Intrauterine contraceptive | ο On the day of removal ο If the IUD is not removed on first day of the patient’s menstrual cycle, additional non-hormonal contraceptive (such as condoms and spermicide) is needed for the first seven days of the first cycle pack.
ο Implant | ο On the day of removal
Complete instructions to facilitate patient counseling on proper tablet usage are located in the FDA-Approved Patient Labeling.

Starting Tri-Lo-Marzia after Abortion or Miscarriage

First-trimester:

- After a first-trimester abortion or miscarriage, Tri-Lo-Marzia may be started immediately. An additional method of contraception is not needed if Tri-Lo-Marzia is started immediately.
- If Tri-Lo-Marzia is not started within 5 days after termination of the pregnancy, the patient should use additional non-hormonal contraception (such as condoms and spermicide) for the first seven days of her first cycle pack of Tri-Lo-Marzia.

Second-trimester:

- Do not start until 4 weeks after a second-trimester abortion or miscarriage, due to the increased risk of thromboembolic disease. Start Tri-Lo-Marzia, following the instructions in Table 1 for Day 1 or Sunday start, as desired. If using Sunday start, use additional non-hormonal contraception (such as condoms and spermicide) for the first seven days of the patient's first cycle pack of Tri-Lo-Marzia. [see CONTRAINDICATIONS (4), WARNINGS AND PRECAUTIONS (5.1), and FDA-APPROVED PATIENT LABELING.]

Starting Tri-Lo-Marzia after Childbirth

- Do not start until 4 weeks after delivery, due to the increased risk of thromboembolic disease. Start contraceptive therapy with Tri-Lo-Marzia following the instructions in Table 1 for women not currently using hormonal contraception.
- Tri-Lo-Marzia is not recommended for use in lactating women [see USE IN SPECIFIC POPULATIONS (8.3)].
- If the woman has not yet had a period postpartum, consider the possibility of ovulation and conception occurring prior to use of Tri-Lo-Marzia. [see CONTRAINDICATIONS (4), WARNINGS AND PRECAUTIONS (5.1), USE IN SPECIFIC POPULATIONS AND (8.1 AND 8.3), and FDA-APPROVED PATIENT LABELING].

Blister Pack:

SET THE DAY

- Sunday Start: Each blister has been preprinted with the days of the week, starting with Sunday, to facilitate a Sunday-Start regimen.
- Day 1 Start:
  - Six different day label strips of the week have been provided with this pack in order to accommodate a Day-1 Start regimen.
  - Pick the day label strip that starts with the first day of your period. Place this day label strip over the area that has the days of the week (starting with Sunday) pre-printed on the blister (Refer figure below).

- Remove pill "1" by pushing down on the pill. The pill will come out through a hole in the back of the strip.
- The patient should wait 24 hours to take the next pill. Continue to take one pill each day until all the pills have been taken.
- When your blister is empty, you will start a new blister on the day after pill "28." The first pill in every refill will always be taken on the same day of the week, no matter when the patient's next period starts.

2.3 Missed Tablets

Table 2: Instructions for Missed Tri-Lo-Marzia Tablets
Ο If one active tablet is missed in Weeks 1, 2, or 3 | Take the tablet as soon as possible. Continue taking one tablet a day until the pack is finished.
Ο If two active tablets are missed in Week 1 or Week 2 | Take the two missed tablets as soon as possible and the next two active tablets the next day. Continue taking one tablet a day until the pack is finished. Additional non-hormonal contraception (such as condoms and spermicide) should be used as backup if the patient has sex within 7 days after missing tablets.
Ο If two active tablets are missed in the third week or three or more active tablets are missed in a row in Weeks 1, 2, or 3 | Day 1 start: Throw out the rest of the pack and start a new pack that same day. Sunday start: Continue taking one tablet a day until Sunday, then throw out the rest of the pack and start a new pack that same day. Additional non-hormonal contraception (such as condoms and spermicide) should be used as back-up if the patient has sex within 7 days after missing tablets.

2.4 Advice in Case of Gastrointestinal Disturbances

In case of severe vomiting or diarrhea, absorption may not be complete and additional contraceptive measures should be taken. If vomiting or diarrhea occurs within 3 to 4 hours after taking an active tablet, handle this as a missed tablet [see FDA-APPROVED PATIENT LABELING].

3 DOSAGE FORMS AND STRENGTHS

Tri-Lo-Marzia Tablets are available in a blister. Each blister contains 28 tablets in the following order:

- 7 white to off white, round, film-coated tablets debossed with 'LU' on one side and "E21" on the other side of the tablet contains 0.18 mg norgestimate and 0.025 mg ethinyl estradiol
- 7 light blue, round, film-coated tablets debossed with 'LU' on one side and "E22" on the other side of the tablet contains 0.215 mg norgestimate and 0.025 mg ethinyl estradiol
- 7 blue, round, film-coated tablets debossed with 'LU' on one side and "E23" on the other side of the tablet contains 0.25 mg norgestimate and 0.025 mg ethinyl estradiol
- 7 green, round, biconvex, film-coated, tablets debossed with 'LU' on one side and "E24" on the other side of the tablet contains inert ingredients

4 CONTRAINDICATIONS

Tri-Lo-Marzia is contraindicated in females who are known to have or develop the following conditions:

- A high risk of arterial or venous thrombotic diseases. Examples include women who are known to:

o Smoke, if over age 35 [see BOXED WARNING and WARNINGS AND PRECAUTIONS (5.1)]

o Have deep vein thrombosis or pulmonary embolism, now or in the past [see WARNINGS AND PRECAUTIONS (5.1)]

o Have inherited or acquired hypercoagulopathies [see WARNINGS AND PRECAUTIONS (5.1)]

o Have cerebrovascular disease [see WARNINGS AND PRECAUTIONS (5.1)]

o Have coronary artery disease [see WARNINGS AND PRECAUTIONS (5.1)]

o Have thrombogenic valvular or thrombogenic rhythm diseases of the heart (for example, subacute bacterial endocarditis with valvular disease, or atrial fibrillation) [see WARNINGS AND PRECAUTIONS (5.1)]

o Have uncontrolled hypertension [see WARNINGS AND PRECAUTIONS (5.4)]

o Have diabetes mellitus with vascular disease [see WARNINGS AND PRECAUTIONS (5.6)]

o Have headaches with focal neurological symptoms or migraine headaches with aura [see WARNINGS AND PRECAUTIONS (5.7)]

o Women over age 35 with any migraine headaches [see WARNINGS AND PRECAUTIONS (5.7)]

- Liver tumors, benign or malignant, or liver disease [see WARNINGS AND PRECAUTIONS (5.2)]
- Undiagnosed abnormal uterine bleeding [see WARNINGS AND PRECAUTIONS (5.8)]
- Pregnancy, because there is no reason to use COCs during pregnancy [see WARNINGS AND PRECAUTIONS (5.9) and USE IN SPECIFIC POPULATIONS (8.1)]
- Current diagnosis of, or history of, breast cancer, which may be hormone-sensitive [see WARNINGS AND PRECAUTIONS (5.11)]
- Use of Hepatitis C drug combinations containing ombitasvir/paritaprevir/ritonavir, with or without dasabuvir, due to the potential for ALT elevations [see WARNINGS AND PRECAUTIONS (5.3)]

5 WARNINGS AND PRECAUTIONS

5.1 Thromboembolic Disorders and Other Vascular Problems

- Stop Tri-Lo-Marzia if an arterial thrombotic event or venous thrombotic (VTE) event occurs.
- Stop Tri-Lo-Marzia if there is unexplained loss of vision, proptosis, diplopia, papilledema, or retinal vascular lesions. Evaluate for retinal vein thrombosis immediately [see ADVERSE REACTIONS (6.2)].
- If feasible, stop Tri-Lo-Marzia at least 4 weeks before and through 2 weeks after major surgery or other surgeries known to have an elevated risk of VTE as well as during and following prolonged immobilization.
- Start Tri-Lo-Marzia no earlier than 4 weeks after delivery, in women who are not breastfeeding. The risk of postpartum VTE decreases after the third postpartum week, whereas the risk of ovulation increases after the third postpartum week.
- The use of COCs increases the risk of VTE. However, pregnancy increases the risk of VTE as much or more than the use of COCs. The risk of VTE in women using COCs is 3 to 9 cases per 10,000 woman-years. The risk of VTE is highest during the first year of use of COCs and when restarting hormonal contraception after a break of 4 weeks or longer. The risk of thromboembolic disease due to COCs gradually disappears after use is discontinued.
- Use of COCs also increases the risk of arterial thromboses such as strokes and myocardial infarctions, especially in women with other risk factors for these events. COCs have been shown to increase both the relative and attributable risks of cerebrovascular events (thrombotic and hemorrhagic strokes). This risk increases with age, particularly in women over 35 years of age who smoke.
- Use COCs with caution in women with cardiovascular disease risk factors.

5.2 Liver Disease

Impaired Liver Function

Do not use Tri-Lo-Marzia in women with liver disease, such as acute viral hepatitis or severe (decompensated) cirrhosis of liver [see CONTRAINDICATIONS (4)]. Acute or chronic disturbances of liver function may necessitate the discontinuation of COC use until markers of liver function return to normal and COC causation has been excluded. Discontinue Tri-Lo-Marzia if jaundice develops.

Liver Tumors

Tri-Lo-Marzia is contraindicated in women with benign and malignant liver tumors [see CONTRAINDICATIONS (4)]. Hepatic adenomas are associated with COC use. An estimate of the attributable risk is 3.3 cases/100,000 COC users. Rupture of hepatic adenomas may cause death through intra-abdominal hemorrhage.

Studies have shown an increased risk of developing hepatocellular carcinoma in long-term (>8 years) COC users. However, the risk of liver cancers in COC users is less than one case per million users.

5.3 Risk of Liver Enzyme Elevations with Concomitant Hepatitis C Treatment

During clinical trials with the Hepatitis C combination drug regimen that contains ombitasvir/paritaprevir/ritonavir, with or without dasabuvir, ALT elevations greater than 5 times the upper limit of normal (ULN), including some cases greater than 20 times the ULN, were significantly more frequent in women using ethinyl estradiol-containing medications, such as COCs. Discontinue Tri-Lo-Marzia prior to starting therapy with the combination drug regimen ombitasvir/paritaprevir/ritonavir, with or without dasabuvir [see CONTRAINDICATIONS (4)]. Tri-Lo-Marzia can be restarted approximately 2 weeks following completion of treatment with the Hepatitis C combination drug regimen.

5.4 High Blood Pressure

Tri-Lo-Marzia is contraindicated in women with uncontrolled hypertension or hypertension with vascular disease [see CONTRAINDICATIONS (4)]. For women with well-controlled hypertension, monitor blood pressure and stop Tri-Lo-Marzia if blood pressure rises significantly.

An increase in blood pressure has been reported in women taking COCs, and this increase is more likely in older women with extended duration of use. The incidence of hypertension increases with increasing concentrations of progestin.

5.5 Gallbladder Disease

Studies suggest a small increased relative risk of developing gallbladder disease among COC users. Use of COCs may worsen existing gallbladder disease. A past history of COC-related cholestasis predicts an increased risk with subsequent COC use. Women with a history of pregnancy-related cholestasis may be at an increased risk for COC related cholestasis.

5.6 Carbohydrate and Lipid Metabolic Effects

Carefully monitor prediabetic and diabetic women who take Tri-Lo-Marzia. COCs may decrease glucose tolerance.

Consider alternative contraception for women with uncontrolled dyslipidemia. A small proportion of women will have adverse lipid changes while on COCs.

Women with hypertriglyceridemia, or a family history thereof, may be at an increased risk of pancreatitis when using COCs.

5.7 Headache

If a woman taking Tri-Lo-Marzia develops new headaches that are recurrent, persistent, or severe, evaluate the cause and discontinue Tri-Lo-Marzia if indicated.

Consider discontinuation of Tri-Lo-Marzia in the case of increased frequency or severity of migraine during COC use (which may be prodromal of a cerebrovascular event).

5.8 Bleeding Irregularities and Amenorrhea

Unscheduled Bleeding and Spotting

Unscheduled (breakthrough or intracyclic) bleeding and spotting sometimes occur in patients on COCs, especially during the first three months of use. If bleeding persists or occurs after previously regular cycles, check for causes such as pregnancy or malignancy. If pathology and pregnancy are excluded, bleeding irregularities may resolve over time or with a change to a different contraceptive product.

In the clinical trial of Tri-Lo-Marzia, the frequency and duration of unscheduled bleeding and/or spotting was assessed in 1,673 women (11,015 evaluable cycles). A total of 3 (0.2%) women discontinued Tri-Lo-Marzia, at least in part, due to bleeding or spotting. Based on data from the clinical trials, 7 to 17% of women using Tri-Lo-Marzia experienced unscheduled bleeding per cycle in the first year. The percent of women who experienced unscheduled bleeding tended to decrease over time.

Amenorrhea and Oligomenorrhea

Women who use Tri-Lo-Marzia may experience amenorrhea. Some women may experience amenorrhea or oligomenorrhea after discontinuation of COCs, especially when such a condition was pre-existent.

If scheduled (withdrawal) bleeding does not occur, consider the possibility of pregnancy. If the patient has not adhered to the prescribed dosing schedule (missed one or more active tablets or started taking them on a day later than she should have), consider the possibility of pregnancy at the time of the first missed period and take appropriate diagnostic measures. If the patient has adhered to the prescribed regimen and misses two consecutive periods, rule out pregnancy.

5.9 COC Use Before or During Early Pregnancy

Extensive epidemiological studies have revealed no increased risk of birth defects in women who have used oral contraceptives prior to pregnancy. Studies also do not suggest a teratogenic effect, particularly in so far as cardiac anomalies and limb reduction defects are concerned, when oral contraceptives are taken inadvertently during early pregnancy. Discontinue Tri-Lo-Marzia use if pregnancy is confirmed.

Administration of COCs to induce withdrawal bleeding should not be used as a test for pregnancy [see USE IN SPECIFIC POPULATIONS (8.1)].

5.10 Depression

Carefully observe women with a history of depression and discontinue Tri-Lo-Marzia if depression recurs to a serious degree.

5.11 Malignant Neoplasms

Breast Cancer

Tri-Lo-Marzia is contraindicated in females who currently have or have had breast cancer because breast cancer may be hormonally sensitive [see CONTRAINDICATIONS (4)].

Epidemiology studies have not found a consistent association between use of combined oral contraceptives (COCs) and breast cancer risk. Studies do not show an association between ever (current or past) use of COCs and risk of breast cancer. However, some studies report a small increase in the risk of breast cancer among current or recent users (<6 months since last use) and current users with longer duration of COC use [see POSTMARKETING EXPERIENCE (6.2)].

Cervical Cancer

Some studies suggest that COC use has been associated with an increase in the risk of cervical cancer or intraepithelial neoplasia. However, there continues to be controversy about the extent to which such findings may be due to differences in sexual behavior and other factors.

5.12 Effect on Binding Globulins

The estrogen component of COCs may raise the serum concentrations of thyroxine-binding globulin, sex hormone-binding globulin, and cortisol-binding globulin. The dose of replacement thyroid hormone or cortisol therapy may need to be increased.

5.13 Monitoring

A woman who is taking COCs should have a yearly visit with her healthcare provider for a blood pressure check and for other indicated healthcare.

5.14 Hereditary Angioedema

In women with hereditary angioedema, exogenous estrogens may induce or exacerbate symptoms of angioedema.

5.15 Chloasma

Chloasma may occasionally occur, especially in women with a history of chloasma gravidarum. Women with a tendency to chloasma should avoid exposure to the sun or ultraviolet radiation while taking Tri-Lo-Marzia.

6 ADVERSE REACTIONS

The following serious adverse reactions with the use of COCs are discussed elsewhere in labeling:

- Serious cardiovascular events and stroke [see BOXED WARNING and WARNINGS AND PRECAUTIONS (5.1)]
- Vascular events [see WARNINGS AND PRECAUTIONS (5.1)]
- Liver disease [see WARNINGS AND PRECAUTIONS (5.2)]

Adverse reactions commonly reported by COC users are:

- Irregular uterine bleeding
- Nausea
- Breast tenderness
- Headache

6.1 Clinical Trial Experience

Because clinical trials are conducted under widely varying conditions, adverse reaction rates observed in the clinical trials of a drug cannot be directly compared to rates in the clinical trials of another drug and may not reflect the rates observed in clinical practice.

The safety of Tri-Lo-Marzia was evaluated in 1,723 subjects who participated in a randomized, partially blinded, multicenter, active-controlled clinical trial of Tri-Lo-Marzia for contraception. This trial examined healthy, nonpregnant, volunteers aged 18 to 45 (nonsmoker if 35 to 45 years of age), who were sexually active with regular coitus. Subjects were followed for up to 13 28-day cycles.

Common Adverse Reactions (≥ 2% of subjects)

The most common adverse reactions reported by at least 2% of the 1,723 women using the 28-day regimen were the following in order of decreasing incidence: headache/migraine (30.5%), nausea/vomiting (16.3%); breast issues (including tenderness, pain, enlargement, swelling, discharge, discomfort, cyst, and nipple pain) (10.3%), abdominal pain (9.2%), menstrual disorders (including dysmenorrhea, menstrual discomfort, menstrual disorder) (9.2%), mood disorders (including depression, mood altered, mood swings and depressed mood) (7.6%); acne (5.1%), vulvovaginal infection (3.5%), abdominal distension (2.8%), weight increased (2.4%), fatigue (2.1%).

Adverse Reactions Leading to Study Discontinuation

In the clinical trial of Tri-Lo-Marzia 4% of subjects discontinued the trial due to an adverse reaction. The most common adverse reactions leading to discontinuation were headache/migraine (1.2%), nausea/vomiting (0.7%), cervical dysplasia (0.7%), abdominal pain (0.4%), ovarian cyst (0.3%), acne (0.2%), flatulence (0.2%) and depression (0.2%).

Serious Adverse Reactions

Carcinoma of the cervix in situ (1 subject) and cervical dysplasia (1 subject).

6.2 Postmarketing Experience

Five studies that compared breast cancer risk between ever-users (current or past use) of COCs and never-users of COCs reported no association between ever use of COCs and breast cancer risk, with effect estimates ranging from 0.90 - 1.12 (Figure 1).

Three studies compared breast cancer risk between current or recent COC users (<6 months since last use) and never users of COCs (Figure 1). One of these studies reported no association between breast cancer risk and COC use. The other two studies found an increased relative risk of 1.19 - 1.33 with current or recent use. Both of these studies found an increased risk of breast cancer with current use of longer duration, with relative risks ranging from 1.03 with less than one year of COC use to approximately 1.4 with more than 8-10 years of COC use.

Figure 1: Risk of Breast Cancer with Combined Oral Contraceptive Use

RR = relative risk; OR = odds ratio; HR = hazard ratio. "ever COC" are females with current or past COC use; "never COC use" are females that never used COCs.

The following additional adverse drug reactions have been reported from worldwide postmarketing experience with norgestimate/ethinyl estradiol. Because these reactions are reported voluntarily from a population of uncertain size, it is not always possible to reliably estimate their frequency or establish a causal relationship to drug exposure.

Infections and Infestations

Urinary tract infection

Neoplasms Benign, Malignant and Unspecified (Including Cysts and Polyps)

Breast cancer, benign breast neoplasm, hepatic adenoma, focal nodular hyperplasia, breast cyst

Immune System Disorders

Hypersensitivity

Metabolism and Nutrition Disorders

Dyslipidemia

Psychiatric Disorders

Anxiety, insomnia

Nervous System Disorders

Syncope, convulsion, paresthesia, dizziness

Eye Disorders

Visual impairment, dry eye, contact lens intolerance

Ear and Labyrinth Disorders

Vertigo

Cardiac Disorders

Tachycardia, palpitations

Vascular Events

Deep vein thrombosis, pulmonary embolism, retinal vascular thrombosis, hot flush

Arterial Events

Arterial thromboembolism, myocardial infarction, cerebrovascular accident

Respiratory, Thoracic and Mediastinal Disorders

Dyspnea

Gastrointestinal Disorders

Pancreatitis, abdominal distension, diarrhea, constipation

Hepatobiliary Disorders

Hepatitis

Skin and Subcutaneous Tissue Disorders

Angioedema, erythema nodosum, hirsutism, night sweats, hyperhidrosis, photosensitivity reaction, urticaria, pruritus, acne

Musculoskeletal, Connective Tissue, and Bone Disorders

Muscle spasms, pain in extremity, myalgia, back pain

Reproductive System and Breast Disorders

Ovarian cyst, suppressed lactation, vulvovaginal dryness

General Disorders and Administration Site Conditions

Chest pain, asthenic conditions.

7 DRUG INTERACTIONS

Consult the labeling of concurrently used drugs to obtain further information about interactions with hormonal contraceptives or the potential for enzyme alterations.

No drug-drug interaction studies were conducted with Tri-Lo-Marzia.

7.1 Effects of Other Drugs on Combined Oral Contraceptives

Substances Decreasing the Plasma Concentrations of COCs

Drugs or herbal products that induce certain enzymes, including cytochrome P450 3A4 (CYP3A4), may decrease the plasma concentrations of COCs and potentially diminish the effectiveness of COCs or increase breakthrough bleeding. Some drugs or herbal products that may decrease the effectiveness of COCs include phenytoin, barbiturates, carbamazepine, bosentan, felbamate, griseofulvin, oxcarbazepine, rifampicin, topiramate, rifabutin, rufinamide, aprepitant and products containing St. John's wort. Interactions between COCs and other drugs may lead to breakthrough bleeding and/or contraceptive failure. Counsel women to use an alternative method of contraception or a back-up method when enzyme inducers are used with COCs, and to continue back-up contraception for 28 days after discontinuing the enzyme inducer to ensure contraceptive reliability.

Colesevelam

Colesevelam, a bile acid sequestrant, given together with a COC, has been shown to significantly decrease the AUC of ethinyl estradiol (EE). The drug interaction between the contraceptive and colesevelam was decreased when the two drug products were given 4 hours apart.

Substances Increasing the Plasma Concentrations of COCs

Co-administration of atorvastatin or rosuvastatin and certain COCs containing EE increase AUC values for EE by approximately 20 to 25%. Ascorbic acid and acetaminophen may increase plasma EE concentrations, possibly by inhibition of conjugation. CYP3A4 inhibitors such as itraconazole, voriconazole, fluconazole, grapefruit juice, or ketoconazole may increase plasma hormone concentrations.

Human Immunodeficiency Virus (HIV)/Hepatitis C Virus (HCV) Protease Inhibitors and Non-nucleoside Reverse Transcriptase Inhibitors

Significant changes (increase or decrease) in the plasma concentrations of estrogen and/or progestin have been noted in some cases of co-administration with HIV protease inhibitors (decrease [e.g., nelfinavir, ritonavir, darunavir/ritonavir, (fos)amprenavir/ritonavir, lopinavir/ritonavir, and tipranavir/ritonavir] or increase [e.g., indinavir and atazanavir/ritonavir])/HCV protease inhibitors (decrease [e.g., boceprevir and telaprevir]) or with non-nucleoside reverse transcriptase inhibitors (decrease [e.g., nevirapine] or increase [e.g., etravirine]).

7.2 Effects of Combined Oral Contraceptives on Other Drugs

- COCs containing EE may inhibit the metabolism of other compounds (e.g., cyclosporine, prednisolone, theophylline, tizanidine, and voriconazole) and increase their plasma concentrations.
- COCs have been shown to decrease plasma concentrations of acetaminophen, clofibric acid, morphine, salicylic acid, temazepam and lamotrigine. Significant decrease in plasma concentration of lamotrigine has been shown, likely due to induction of lamotrigine glucuronidation. This may reduce seizure control; therefore, dosage adjustments of lamotrigine may be necessary.

Women on thyroid hormone replacement therapy may need increased doses of thyroid hormone because the serum concentration of thyroid-binding globulin increases with use of COCs.

7.3 Interference with Laboratory Tests

The use of contraceptive steroids may influence the results of certain laboratory tests, such as coagulation factors, lipids, glucose tolerance, and binding proteins.

7.4 Concomitant Use with HCV Combination Therapy – Liver Enzyme Elevation

Do not co-administer Tri-Lo-Marzia Tablets with HCV drug combinations containing ombitasvir/paritaprevir/ritonavir, with or without dasabuvir, due to potential for ALT elevations [see WARNINGS AND PRECAUTIONS (5.3)].

8 USE IN SPECIFIC POPULATIONS

8.1 Pregnancy

There is little or no increased risk of birth defects in women who inadvertently use COCs during early pregnancy. Epidemiologic studies and meta-analyses have not found an increased risk of genital or non-genital birth defects (including cardiac anomalies and limb reduction defects) following exposure to low dose COCs prior to conception or during early pregnancy.

Do not administer COCs to induce withdrawal bleeding as a test for pregnancy. Do not use COCs during pregnancy to treat threatened or habitual abortion.

8.3 Nursing Mothers

Advise the nursing mother to use other forms of contraception, when possible, until she has weaned her child. COCs can reduce milk production in breastfeeding mothers. This is less likely to occur once breastfeeding is well-established; however, it can occur at any time in some women. Small amounts of oral contraceptive steroids and/or metabolites are present in breast milk.

8.4 Pediatric Use

Safety and efficacy of Tri-Lo-Marzia Tablets have been established in women of reproductive age. Efficacy is expected to be the same for post-pubertal adolescents under the age of 18 and for users 18 years and older. Use of this product before menarche is not indicated.

8.5 Geriatric Use

Tri-Lo-Marzia has not been studied in postmenopausal women and is not indicated in this population.

8.6 Hepatic Impairment

The pharmacokinetics of Tri-Lo-Marzia has not been studied in subjects with hepatic impairment. However, steroid hormones may be poorly metabolized in patients with hepatic impairment. Acute or chronic disturbances of liver function may necessitate the discontinuation of COC use until markers of liver function return to normal and COC causation has been excluded. [see CONTRAINDICATIONS (4) and WARNINGS AND PRECAUTIONS (5.2).]

8.7 Renal Impairment

The pharmacokinetics of Tri-Lo-Marzia has not been studied in women with renal impairment.

10 OVERDOSAGE

There have been no reports of serious ill effects from overdosage of oral contraceptives, including ingestion by children. Overdosage may cause withdrawal bleeding in females and nausea.

11 DESCRIPTION

Tri-Lo-Marzia is a combination oral contraceptive containing the progestational compound norgestimate and the estrogenic compound ethinyl estradiol. Norgestimate is designated as ((+)-13-Ethyl-17-hydroxy-18, 19-dinor-17a-pregn-4-en-20-yn-3-one oxime acetate (ester)) and ethinyl estradiol is designated as (19-nor-17a-pregna,1,3,5(10)-trien-20-yne-3,17-diol).

- Each active white film-coated tablet contains 0.18 mg norgestimate and 0.025 mg ethinyl estradiol. Inactive ingredients include anhydrous lactose, croscarmellose sodium, hypromellose, lactose monohydrate, magnesium stearate, microcrystalline cellulose, polyethylene glycol, povidone and titanium dioxide.
- Each active light blue film-coated tablet contains 0.215 mg norgestimate and 0.025 mg ethinyl estradiol. Inactive ingredients include anhydrous lactose, croscarmellose sodium, FD&C Blue No. 2 Aluminium Lake, hypromellose, lactose monohydrate, magnesium stearate, microcrystalline cellulose, polyethylene glycol, povidone and titanium dioxide.
- Each active blue film-coated tablet contains 0.25 mg norgestimate and 0.025 mg ethinyl estradiol. Inactive ingredients include anhydrous lactose, croscarmellose sodium, FD&C Blue No. 2 Aluminium Lake, hypromellose, lactose monohydrate, magnesium stearate, microcrystalline cellulose, polyethylene glycol, povidone and titanium dioxide.
- Each green film-coated tablet contains only inert ingredients, as follows: croscarmellose sodium, FD&C Blue No. 2 Aluminium Lake, hypromellose, iron oxide yellow, lactose monohydrate, magnesium stearate, microcrystalline cellulose, polyethylene glycol and titanium dioxide.

12 CLINICAL PHARMACOLOGY

12.1 Mechanism of Action

COCs lower the risk of becoming pregnant primarily by suppressing ovulation. Other possible mechanisms may include cervical mucus changes that inhibit sperm penetration and endometrial changes that reduce the likelihood of implantation.

12.2 Pharmacodynamics

No specific pharmacodynamic studies were conducted with Tri-Lo-Marzia.

12.3 Pharmacokinetics

Absorption

Norgestimate (NGM) and EE are rapidly absorbed following oral administration. NGM is rapidly and completely metabolized by first pass (intestinal and/or hepatic) mechanisms to norelgestromin (NGMN) and norgestrel (NG), which are the major active metabolites of NGM.

Mean pharmacokinetic parameters for NGMN, NG and EE during three cycles of administration of Tri-Lo-Marzia are summarized in Table 3.

Peak serum concentrations of NGMN and EE were generally reached by 2 hours after administration of Tri-Lo-Marzia. Accumulation following multiple dosing of the 0.18 mg NGM / 0.025 mg EE dose is approximately 1.5 to 2 fold for NGMN and approximately 1.5 fold for EE compared with single dose administration, in agreement with that predicted based on linear kinetics of NGMN and EE. The pharmacokinetics of NGMN is dose proportional following NGM doses of 0.18 to 0.25 mg. Steady-state conditions for NGMN following each NGM dose and for EE were achieved during the three cycle study. Non-linear accumulation (4.5 to 14.5 fold) of NG was observed as a result of high affinity binding to SHBG, which limits its biological activity.

Table 3 Summary of NGMN, NG and EE pharmacokinetic parameters.

Table 3: Mean (SD) Pharmacokinetic Parameters of Tri-Lo-Marzia During a Three Cycle Study
Analyte [NGMN = Norelgestromin, NG = norgestrel, EE = ethinyl estradiol] | Cycle | Day | Cmax | tmax (h) | AUC0 to 24h | t1/2 (h)
NGMN ([Cmax = peak serum concentration, tmax = time to reach peak serum concentration, AUC0to24h= area under serum concentration vs. time curve from 0 to 24 hours, t1/2= elimination half-life.] to [units for NGMN and NG - Cmax = ng/mL, AUC0to24h= h.ng/mL]) | 1 | 1 | 0.91 (0.27) | 1.8 (1.0) | 5.86 (1.54) | NC
 | 3 | 7 | 1.42 (0.43) | 1.8 (0.7) | 11.3 (3.2) | NC
 |  | 14 | 1.57 (0.39) | 1.8 (0.7) | 13.9 (3.7) | NC
 |  | 21 | 1.82 (0.54) | 1.5 (0.7) | 16.1 (4.8) | 28.1 (10.6)
NG (to) | 1 | 1 | 0.32 (0.14) | 2.0 (1.1) | 2.44 (2.04) | NC
 | 3 | 7 | 1.64 (0.89) | 1.9 (0.9) | 27.9 (18.1) | NC
 |  | 14 | 2.11 (1.13) | 4.0 (6.3) | 40.7 (24.8) | NC
 |  | 21 | 2.79 (1.42) | 1.7 (1.2) | 49.9 (27.6) | 36.4 (10.2)
EE (, [units for all analytes; h = hours] , [units for EE only - Cmax = pg/mL, AUC0to24h= h.pg/mL]) | 1 | 1 | 55.6 (18.1) | 1.7 (0.5) | 421 (118) | NC
 | 3 | 7 | 91.1 (36.7) | 1.3 (0.3) | 782 (329) | NC
 |  | 14 | 96.9 (38.5) | 1.3 (0.3) | 796 (273) | NC
 |  | 21 | 95.9 (38.9) | 1.3 (0.6) | 771 (303) | 17.7 (4.4)
NC = not calculated

Food Effect:

The effect of food on the pharmacokinetics of Tri-Lo-Marzia has not been studied.

Distribution

NGMN and NG are highly bound (>97%) to serum proteins. NGMN is bound to albumin and not to SHBG, while NG is bound primarily to SHBG. EE is extensively bound (>97%) to serum albumin and induces an increase in the serum concentrations of SHBG.

Metabolism

NGM is extensively metabolized by first-pass mechanisms in the gastrointestinal tract and/or liver. NGM's primary active metabolite is NGMN. Subsequent hepatic metabolism of NGMN occurs and metabolites include NG, which is also active and various hydroxylated and conjugated metabolites. Although NGMN and its metabolites inhibit a variety of P450 enzymes in human liver microsomes, under the recommended dosing regimen, the in vivo concentrations of NGMN and its metabolites, even at the peak serum levels, are relatively low compared to the inhibitory constant (Ki). EE is also metabolized to various hydroxylated products and their glucuronide and sulfate conjugates.

Excretion

Following 3 cycles of administration of Tri-Lo-Marzia, the mean (± SD) elimination half-life values, at steady-state, for NGMN, NG and EE were 28.1 (± 10.6) hours, 36.4 (± 10.2) hours and 17.7 (± 4.4) hours, respectively (Table 2). The metabolites of NGMN and EE are eliminated by renal and fecal pathways.

Use in Specific Populations

Effects of Body Weight, Body Surface Area, and Age:

The effects of body weight, body surface area, age and race on the pharmacokinetics of NGMN, NG and EE were evaluated in 79 healthy women using pooled data following single dose administration of NGM 0.18 or 0.25 mg / EE 0.025 mg tablets in four pharmacokinetic studies. Increasing body weight and body surface area were each associated with decreases in Cmax and AUC0 to 24h values for NGMN and EE and increases in CL/F (oral clearance) for EE. Increasing body weight by 10 kg is predicted to reduce the following parameters: NGMN Cmax by 9% and AUC0 to 24h by 19%, NG Cmax by 12% and AUC0 to 24h by 46%, EE Cmax by 13% and AUC0 to 24h by 12%. These changes were statistically significant. Increasing age was associated with slight decreases (6% with increasing age by 5 years) in Cmax and AUC0 to 24h for NGMN and were statistically significant, but there was no significant effect for NG or EE. Only a small to moderate fraction (5 to 40%) of the overall variability in the pharmacokinetics of NGMN and EE following Tri-Lo-Marzia Tablets may be explained by any or all of the above demographic parameters.

13 NONCLINICAL TOXICOLOGY

13.1 Carcinogenesis, Mutagenesis, Impairment of Fertility

[see WARNINGS AND PRECAUTIONS (5.2, 5.11) and USE IN SPECIFIC POPULATIONS (8.1).

14 CLINICAL STUDIES

In an active controlled clinical trial lasting 12 months, 1,673 women, 18 to 45 years old completed 11,003 cycles of Tri-Lo-Marzia use and a total of 20 pregnancies were reported in Tri-Lo-Marzia users. The racial demographic of those treated with Tri-Lo-Marzia was: Caucasian (86%), African-American (6%), Asian (2%), and Other (6%). There were no exclusions on the basis of weight; the weight range for women treated was 90 to 240 lbs, with a mean weight of about 142 lbs. The pregnancy rate in women aged 18 to 35 years was approximately 2.6 pregnancies per 100 woman-years of use.

16 HOW SUPPLIED/STORAGE AND HANDLING

16.1 How Supplied

Tri-Lo-Marzia are available in a blister (NDC 68180-837-71) containing 28 tablets packed in a pouch (NDC 68180-837-71). Such three pouches are packaged in a carton (NDC 68180-837-73).

Each blister (28 tablets) contains in the following order:

- 7 white to off white, round, film-coated tablets debossed with 'LU' on one side and "E21" on the other side contains 0.18 mg norgestimate and 0.025 mg ethinyl estradiol
- 7 light blue, round, film-coated tablets debossed with 'LU' on one side and "E22" on the other side contains 0.215 mg norgestimate and 0.025 mg ethinyl estradiol
- 7 blue, round, film-coated tablets debossed with 'LU' on one side and "E23" on the other side contains 0.25 mg norgestimate and 0.025 mg ethinyl estradiol
- 7 green, round, biconvex, film-coated tablets (non-hormonal placebo) debossed with 'LU' on one side and "E24" on the other side contains inert ingredients

16.2 Storage Conditions

- Store at 25°C (77°F); excursions permitted to 15° to 30°C (59° to 86°F). [see USP Controlled Room Temperature].
- Protect from light.
- Keep this and all medication out of reach of children.

17 PATIENT COUNSELING INFORMATION

See FDA-APPROVED PATIENT LABELING (PATIENT INFORMATION and INSTRUCTION FOR USE).

Counsel patients about the following information:

- Cigarette smoking increases the risk of serious cardiovascular events from COC use, and that women who are over 35 years old and smoke should not use COCs [see BOXED WARNING].
- Increased risk of VTE compared to non-users of COCs is greatest after initially starting a COC or restarting (following a 4-week or greater pill-free interval) the same or a different COC [see WARNINGS AND PRECAUTIONS (5.1)].
- Tri-Lo-Marzia does not protect against HIV infection (AIDS) and other sexually transmitted infections.
- Tri-Lo-Marzia is not to be used during pregnancy; if pregnancy occurs during use of Tri-Lo-Marzia instruct the patient to stop further use [see WARNINGS AND PRECAUTIONS (5.9)].
- Take one tablet daily by mouth at the same time every day. Instruct patients what to do in the event tablets are missed [see DOSAGE AND ADMINISTRATION (2.2)].
- Use a back-up or alternative method of contraception when enzyme inducers are used with Tri-Lo-Marzia [see DRUG INTERACTIONS (7.1)].
- COCs may reduce breast milk production, this is less likely to occur if breastfeeding is well established [see USE IN SPECIFIC POPULATIONS (8.3)].
- Women who start COCs postpartum; and who have not yet had a period, should use an additional method of contraception until they have taken a white tablet for 7 consecutive days [see DOSAGE AND ADMINISTRATION (2.2)].
- Amenorrhea may occur. Consider pregnancy in the event of amenorrhea at the time of the first missed period. Rule out pregnancy in the event of amenorrhea in two or more consecutive cycles [see WARNINGS AND PRECAUTIONS (5.8)].

Distributed by:

Lupin Pharmaceuticals, Inc.

Naples, FL 34108

United States

Manufactured by:

Lupin Limited

Pithampur (M.P.) - 454 775

India

Revised: November 2024

PATIENT INFORMATION

PATIENT INFORMATION

Tri-Lo-Marzia™ [TRY-LOW-mar-ZEE-uh]

(norgestimate and ethinyl estradiol tablets USP)

What is the most important information I should know about Tri-Lo-Marzia?

Do not use Tri-Lo-Marzia if you smoke cigarettes and are over 35 years old. Smoking increases your risk of serious cardiovascular side effects from hormonal birth control pills, including death from heart attack, blood clots or stroke. This risk increases with age and the number of cigarettes you smoke.

What is Tri-Lo-Marzia?

Tri-Lo-Marzia is a birth control pill (oral contraceptive) used by women to prevent pregnancy.

How does Tri-Lo-Marzia work for contraception?

Your chance of getting pregnant depends on how well you follow the directions for taking your birth control pills. The better you follow the directions, the less chance you have of getting pregnant.

Based on the results from the clinical study, about 3 out of 100 women may get pregnant during the first year they use Tri-Lo-Marzia.

The following chart shows the chance of getting pregnant for women who use different methods of birth control. Each box on the chart contains a list of birth control methods that are similar in effectiveness. The most effective methods are at the top of the chart. The box on the bottom of the chart shows the chance of getting pregnant for women who do not use birth control and are trying to get pregnant.

Who should not take Tri-Lo-Marzia?

Do not take Tri-Lo-Marzia if you:

- smoke and are over 35 years of age
- had blood clots in your arms, legs, lungs, or eyes
- had a problem with your blood that makes it clot more than normal
- have certain heart valve problems or irregular heart beat that increases your risk of having blood clots
- had a stroke
- had a heart attack
- have high blood pressure that cannot be controlled by medicine
- have diabetes with kidney, eye, nerve, or blood vessel damage
- have certain kinds of severe migraine headaches with aura, numbness, weakness or changes in vision, or any migraine headaches if you are over 35 years of age
- have liver problems, including liver tumors
- take any Hepatitis C drug combination containing ombitasvir/paritaprevir/ ritonavir, with or without dasabuvir. This may increase levels of the liver enzyme "alanine aminotransferase" (ALT) in the blood.
- have any unexplained vaginal bleeding
- are pregnant
- had breast cancer or any cancer that is sensitive to female hormones

If any of these conditions happen while you are taking Tri-Lo-Marzia, stop taking Tri-Lo-Marzia right away and talk to your healthcare provider. Use non-hormonal contraception when you stop taking Tri-Lo-Marzia.

What should I tell my healthcare provider before taking Tri-Lo-Marzia?

Tell your healthcare provider if you:

- are pregnant or think you may be pregnant
- are depressed now or have been depressed in the past
- had yellowing of your skin or eyes (jaundice) caused by pregnancy (cholestasis of pregnancy)
- are breastfeeding or plan to breastfeed. Tri-Lo-Marzia may decrease the amount of breast milk you make. A small amount of the hormones in Tri-Lo-Marzia may pass into your breast milk. Talk to your healthcare provider about the best birth control method for you while breastfeeding.

Tell your healthcare provider about all the medicines you take, including prescription and over-the-counter medicines, vitamins and herbal supplements.

Tri-Lo-Marzia may affect the way other medicines work, and other medicines may affect how well Tri-Lo-Marzia works.

Know the medicines you take. Keep a list of them to show your healthcare provider and pharmacist when you get a new medicine.

How should I take Tri-Lo-Marzia?

Read the Instructions for Use at the end of this Patient Information.

What are the possible serious side effects of Tri-Lo-Marzia?

- Like pregnancy, Tri-Lo-Marzia may cause serious side effects, including blood clots in your lungs, heart attack, or a stroke that may lead to death. Some other examples of serious blood clots include blood clots in the legs or eyes.

Serious blood clots can happen especially if you smoke, are obese, or are older than 35 years of age. Serious blood clots are more likely to happen when you:

- first start taking birth control pills
- restart the same or different birth control pills after not using them for a month or more

Call your healthcare provider or go to a hospital emergency room right away if you have:

- leg pain that will not go away
- sudden severe shortness of breath
- sudden change in vision or blindness
- chest pain
- a sudden, severe headache unlike your usual headaches
- weakness or numbness in your arm or leg
- trouble speaking

Other serious side effects include:

- liver problems, including:
  - rare liver tumors
  - jaundice (cholestasis), especially if you previously had cholestasis of pregnancy. Call your healthcare provider if you have yellowing of your skin or eyes

- high blood pressure . You should see your healthcare provider for a yearly check of your blood pressure.
- gallbladder problems
- changes in the sugar and fat (cholesterol and triglycerides) levels in your blood
- new or worsening headaches including migraine headaches
- irregular or unusual vaginal bleeding and spotting between your menstrual periods, especially during the first 3 months of taking Tri-Lo-Marzia.
- depression
- possible cancer in your breast and cervix
- swelling of your skin especially around your mouth, eyes, and in your throat (angioedema). Call your healthcare provider if you have a swollen face, lips, mouth tongue or throat, which may lead to difficulty swallowing or breathing. Your chance of having angioedema is higher is you have a history of angioedema.
- dark patches of skin around your forehead, nose, cheeks and around your mouth, especially during pregnancy (chloasma). Women who tend to get chloasma should avoid spending a long time in sunlight, tanning booths, and under sun lamps while taking Tri-Lo-Marzia. Use sunscreen if you have to be in the sunlight.

What are the most common side effects of Tri-Lo-Marzia?

- headache (including migraine)
- nausea and vomiting
- breast problems
  - tenderness, pain and discomfort
  - enlargement and swelling
  - discharge
  - nipple pain
- stomach pain
- pain with your periods (menstrual cycle)
- mood changes, including depression
- acne
- vaginal infections
- bloating
- weight gain
- fatigue

These are not all the possible side effects of Tri-Lo-Marzia. For more information, ask your healthcare provider or pharmacist.

You may report side effects to the FDA at 1-800-FDA-1088.

You may also report side effects to Lupin Pharmaceuticals, Inc. at 1-800-399-2561 or you can visit the Lupin website at www.lupinpharmaceuticals.com.

What else should I know about taking Tri-Lo-Marzia?

- If you are scheduled for any lab tests, tell your healthcare provider you are taking Tri-Lo-Marzia. Certain blood tests may be affected by Tri-Lo-Marzia.
- Tri-Lo-Marzia does not protect against HIV infection (AIDS) and other sexually transmitted infections.

How should I store Tri-Lo-Marzia?

- Store Tri-Lo-Marzia at room temperature between 68° to 77°F (20° to 25°C).
- Keep Tri-Lo-Marzia and all medicines out of the reach of children.
- Store away from light.

General information about the safe and effective use of Tri-Lo-Marzia.

Medicines are sometimes prescribed for purposes other than those listed in a Patient Information leaflet. Do not use Tri-Lo-Marzia for a condition for which it was not prescribed. Do not give Tri-Lo-Marzia to other people, even if they have the same symptoms that you have.

This Patient Information summarizes the most important information about Tri-Lo-Marzia. You can ask your pharmacist or healthcare provider for information about Tri-Lo-Marzia that is written for health professionals.

For more information, call Lupin Pharmaceuticals, Inc. at 1-800-399-2561 or you can visit the Lupin website at www.lupinpharmaceuticals.com.

Does hormonal birth control cause cancer?

It is not known if hormonal birth control pills causes breast cancer. Some studies, but not all, suggest that there could be a slight increase in the risk of breast cancer among current users with longer duration of use.

If you have breast cancer now, or have had it in the past, do not use hormonal birth control because some breast cancers are sensitive to hormones.

Women who use birth control pills may have a slightly higher chance of getting cervical cancer. However, this may be due to other reasons such as having more sexual partners.

What if I want to become pregnant?

You may stop taking the pill whenever you wish. Consider a visit with your healthcare provider for a pre-pregnancy checkup before you stop taking the pill.

What should I know about my period when taking Tri-Lo-Marzia?

Your periods may be lighter and shorter than usual. Some women may miss a period. Irregular vaginal bleeding or spotting may happen while you are taking Tri-Lo-Marzia, especially during the first few months of use. This usually is not a serious problem. It is important to continue taking your pills on a regular schedule to prevent a pregnancy.

What are the ingredients in Tri-Lo-Marzia?

Active ingredients: Each white to off white, light blue, and blue pill contains norgestimate and ethinyl estradiol.

Inactive ingredients:

White to off white pills: anhydrous lactose, croscarmellose sodium, hypromellose, lactose monohydrate, magnesium stearate, microcrystalline cellulose, polyethylene glycol, povidone and titanium dioxide.

Light blue pills: anhydrous lactose, croscarmellose sodium, FD&C Blue No. 2 Aluminium Lake, hypromellose, lactose monohydrate, magnesium stearate, microcrystalline cellulose, polyethylene glycol, povidone and titanium dioxide.

Blue pills: anhydrous lactose, croscarmellose sodium, FD&C Blue No. 2 Aluminium Lake, hypromellose, lactose monohydrate, magnesium stearate, microcrystalline cellulose, polyethylene glycol, povidone and titanium dioxide.

Green pills: croscarmellose sodium, FD&C Blue No. 2 Aluminium Lake, hypromellose, iron oxide yellow, lactose monohydrate, magnesium stearate, microcrystalline cellulose, polyethylene glycol and titanium dioxide.

INSTRUCTIONS OF USE

Tri-Lo-Marzia [TRY-LOW-mar-ZEE-uh]

(norgestimate and ethinyl estradiol tablets USP)

Important Information about taking Tri-Lo-Marzia

- Take 1 pill every day at the same time. Take the pills in the order directed on your blister.
- Do not skip your pills, even if you do not have sex often. If you miss pills (including starting the pack late) you could get pregnant . The more pills you miss, the more likely you are to get pregnant.
- If you have trouble remembering to take Tri-Lo-Marzia, talk to your healthcare provider. When you first start taking Tri-Lo-Marzia, spotting or light bleeding in between your periods may occur. Contact your healthcare provider if this does not go away after a few months.
- You may feel sick to your stomach (nauseous), especially during the first few months of taking Tri-Lo-Marzia. If you feel sick to your stomach, do not stop taking the pill. The problem will usually go away. If your nausea does not go away, call your healthcare provider.
- Missing pills can also cause spotting or light bleeding, even when you take the missed pills later. On the days you take 2 pills to make up for missed pills (see What should I do if I miss any Tri-Lo-Marzia pills? below), you could also feel a little sick to your stomach.
- It is not uncommon to miss a period. However, if you miss a period and have not taken Tri-Lo-Marzia according to directions, or miss 2 periods in a row, or feel like you may be pregnant, call your healthcare provider. If you have a positive pregnancy test, you should stop taking Tri-Lo-Marzia.
- If you have vomiting or diarrhea within 3 to 4 hours of taking your pill, take another pill of the same color from your extra blister. If you do not have an extra blister, take the next pill in your blister. Continue taking all your remaining pills in order. Start the first pill of your next blister the day after finishing your current blister. This will be 1 day earlier than originally scheduled. Continue on your new schedule.
- If you have vomiting or diarrhea for more than 1 day, your birth control pills may not work as well. Use an additional birth control method, like condoms and a spermicide, until you check with your healthcare provider.
- Stop taking Tri-Lo-Marzia at least 4 weeks before you have major surgery and do not restart after the surgery without asking your healthcare provider. Be sure to use other forms of contraception (like condoms and spermicide) during this time period.

Before you start taking Tri-Lo-Marzia:

- Decide what time of day you want to take your pill. It is important to take it at the same time every day and in the order as directed on your blister.
- Have backup contraception (condoms and spermicide) available and if possible, an extra full pack of pills as needed.

When should I start taking Tri-Lo-Marzia?

If you start taking Tri-Lo-Marzia and you have not used a hormonal birth control method before:

- There are 2 ways to start taking your birth control pills. You can either start on a Sunday (Sunday Start) or on the first day (Day 1) of your natural menstrual period (Day 1 Start). Your healthcare provider should tell you when to start taking your birth control pill.
- If you use the Sunday Start, use non-hormonal back-up contraception such as condoms and spermicide for the first 7 days that you take Tri-Lo-Marzia. You do not need back-up contraception if you use the Day 1 Start.

If you start taking Tri-Lo-Marzia and you are switching from another birth control pill:

- Start your new Tri-Lo-Marzia pack on the same day that you would start the next pack of your previous birth control method.
- Do not continue taking the pills from your previous birth control pack.

If you start taking Tri-Lo-Marzia and previously used a vaginal ring or transdermal patch:

- Start using Tri-Lo-Marzia on the day you would have reapplied the next ring or patch.

If you start taking Tri-Lo-Marzia and you are switching from a progestin-only method such as an implant or injection:

- Start taking Tri-Lo-Marzia on the day of removal of your implant or on the day when you would have had your next injection.

If you start taking Tri-Lo-Marzia and you are switching from an intrauterine device or system (IUD or IUS):

- Start taking Tri-Lo-Marzia on the day of removal of your IUD or IUS.
- You do not need back-up contraception if your IUD or IUS is removed on the first day (Day 1) of your period. If your IUD or IUS is removed on any other day, use non-hormonal back-up contraception such as condoms and spermicide for the first 7 days that you take Tri-Lo-Marzia.

Keep a calendar to track your period:

If this is the first time you are taking birth control pills, read, "When should I start taking Tri-Lo-Marzia?" above. Follow these instructions for either a Sunday Start or a Day 1 Start.

Sunday Start:

You will use a Sunday Start if your healthcare provider told you to take your first pill on a Sunday.

- Take pill 1 on the Sunday after your period starts .
- If your period starts on a Sunday, take pill "1 " that day and refer to Day 1 Start instructions below.
- Take 1 pill every day in the order on the blister at the same time each day for 28 days.
- After taking the last pill on Day 28 from the blister, start taking the first pill from a new pack, on the same day of the week as the first pack (Sunday). Take the first pill in the new pack whether or not you are having your period.
- Use non-hormonal back-up contraception such as condoms and spermicide for the first 7 days of the first cycle that you take Tri-Lo-Marzia.

Day 1 Start:

You will use a Day 1 Start if your doctor told you to take your first pill (Day 1) on the first day of your period.

- Take 1 pill every day in the order of the blister, at the same time each day, for 28 days.
- After taking the last pill on Day 28 from the blister, start taking the first pill from a new pack, on the same day of the week as the first pack. Take the first pill in the new pack whether or not you are having your period.

Instructions for using your blister:

Each new blister has 28 pills

- 7 white to off white pills with hormone, for Days 1 to 7
- 7 light blue pills with hormone, for Days 8 to 14
- 7 blue pills with hormones, for Days 15 to 21
- 7 green pills (without hormones), for Days 22 to 28 .

Step 1. SET THE DAY on your Blister

Sunday Start: Each blister has been preprinted with the days of the week, starting with Sunday, to facilitate a Sunday-Start regimen.

Day 1 Start:

- Six different day label strips of the week have been provided with this pack in order to accommodate a Day-1 Start regimen.
- Pick the day label strip that starts with the first day of your period. Place this day label strip over the area that has the days of the week (starting with Sunday) pre-printed on the blister (Refer figure below).

Step 2. Remove pill "1" by pushing down on the pill. The pill will come out through a hole in the back of the strip.

Step 3. Swallow the pill. You will take 1 pill every day, at the same time each day.

Step 4. Wait 24 hours to take your next pill. Continue to take 1 pill each day until all the pills have been taken.

Step 5. Take your pill at the same time every day. It is important to take the correct pill each day and not miss any pills.

To help you remember, take your pill at the same time as another daily activity, like turning off your alarm clock or brushing your teeth.

Step 6. When your blister is empty. You will start a new blister on the day after pill "28." Remember to take your first pill in every refill on the same day of the week, no matter when your next period starts.

What should I do if I miss any Tri-Lo-Marzia pills?

If you miss 1 pill in Weeks 1, 2, or 3, follow these steps:

- Take it as soon as you remember. Take the next pill at your regular time. This means you may take 2 pills in 1 day.
- Then continue taking 1 pill every day until you finish the pack.
- You do not need to use a back-up birth control method if you have sex.

If you miss 2 pills in Week 1 or Week 2 of your pack, follow these steps:

- Take the 2 missed pills as soon as possible and the next 2 pills the next day.
- Then continue to take 1 pill every day until you finish the pack.
- Use a non-hormonal birth control method (such as a condom and spermicide) as a back-up if you have sex during the first 7 days after missing your pills.

If you miss 2 pills in a row in Week 3, or you miss 3 or more pills in a row during Weeks 1, 2, or 3 of the pack, follow these steps:

- If you are a Day 1 Starter:
- Throw out the rest of the pill pack and start a new pack that same day.
- You may not have your period this month but this is expected. However, if you miss your period 2 months in a row, call your healthcare provider because you might be pregnant.
- You could become pregnant if you have sex during the first 7 days after you restart your pills. You MUST use a non-hormonal birth control method (such as a condom and spermicide) as a back-up if you have sex during the first 7 days after you restart your pills.

- If you are a Sunday Starter:
- Keep taking 1 pill every day until Sunday. On Sunday, throw out the rest of the pack and start a new pack of pills that same day.
- Use a non-hormonal birth control method (such as a condom and spermicide) as a back-up if you have sex during the first 7 days after you restart your pills.

If you have any questions or are unsure about the information in this leaflet, call your healthcare provider.

Distributed by:

Lupin Pharmaceuticals, Inc.

Naples, FL 34108

United States

Manufactured by:

Lupin Limited

Pithampur (M.P.) - 454 775

India

This Patient Information and Instructions for Use has been approved by the U.S. Food and Drug Administration.

Revised: November 2024 ID#: 277632

PACKAGE LABEL.PRINCIPAL DISPLAY PANEL

TRI-LO-MARZIA™ (norgestimate and ethinyl estradiol tablets USP)

0.18 mg 0.025 mg, 0.215 mg 0.025 mg, 7 0.25 mg 0.025 mg

28 Day Regimen

Blister Pack:

NDC: 68180-837-71

28 Tablets

TRI-LO-MARZIA™ (norgestimate and ethinyl estradiol tablets USP)

0.18 mg 0.025 mg, 0.215 mg 0.025 mg, 7 0.25 mg 0.025 mg

28 Day Regimen

Pouch:

NDC: 68180-837-71

28 Tablets

TRI-LO-MARZIA™ (norgestimate and ethinyl estradiol tablets USP)

0.18 mg 0.025 mg, 0.215 mg 0.025 mg, 7 0.25 mg 0.025 mg

28 Day Regimen

Carton Pack:

NDC: 68180-837-73

3 Blisters of 28 Tablets Each